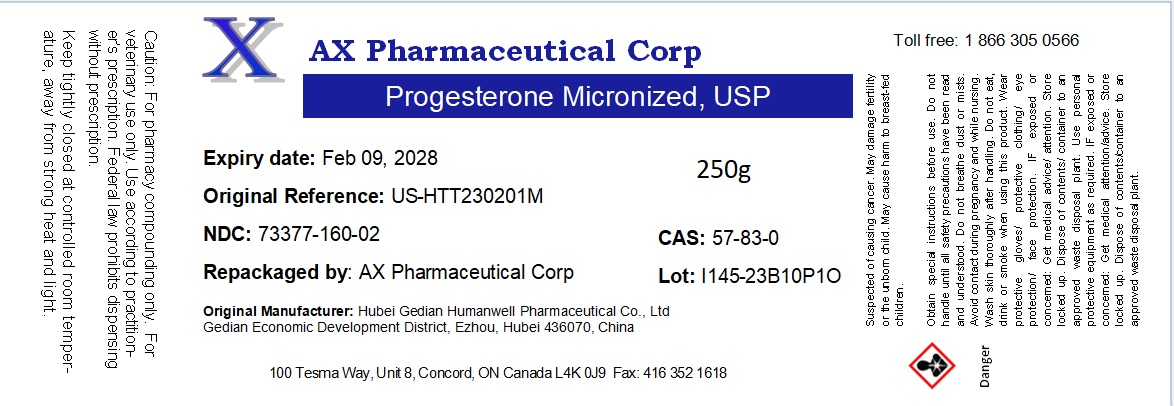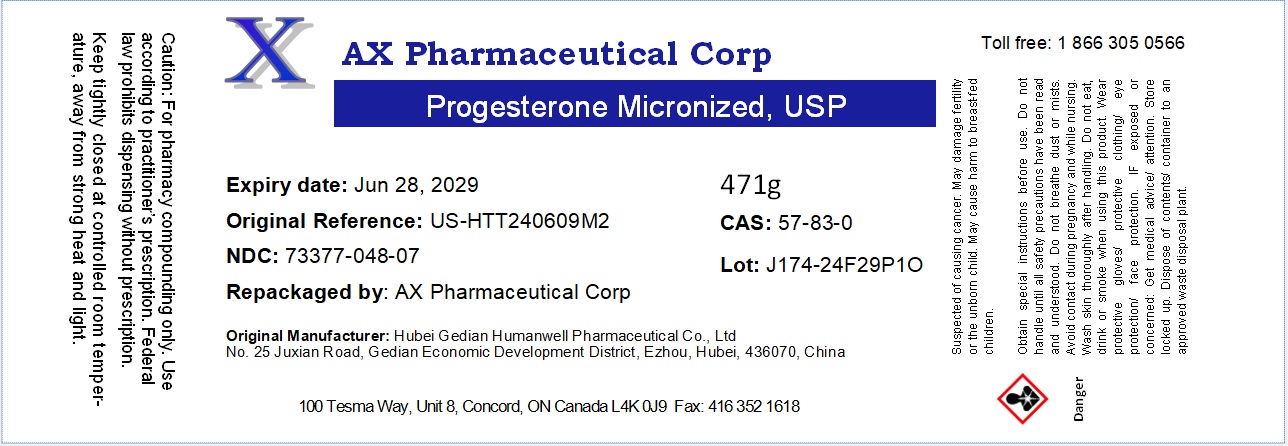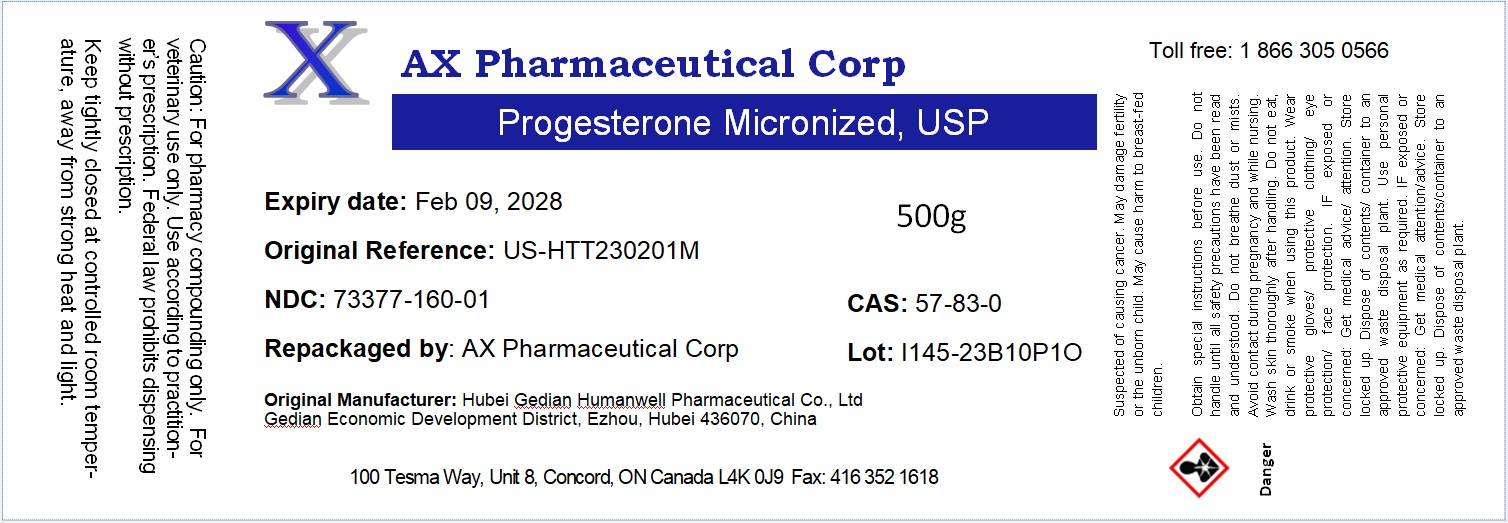 DRUG LABEL: Progesterone
NDC: 73377-160 | Form: POWDER
Manufacturer: AX Pharmaceutical Corp
Category: other | Type: BULK INGREDIENT - ANIMAL DRUG
Date: 20241219

ACTIVE INGREDIENTS: Progesterone 1 g/1 g

Progesterone